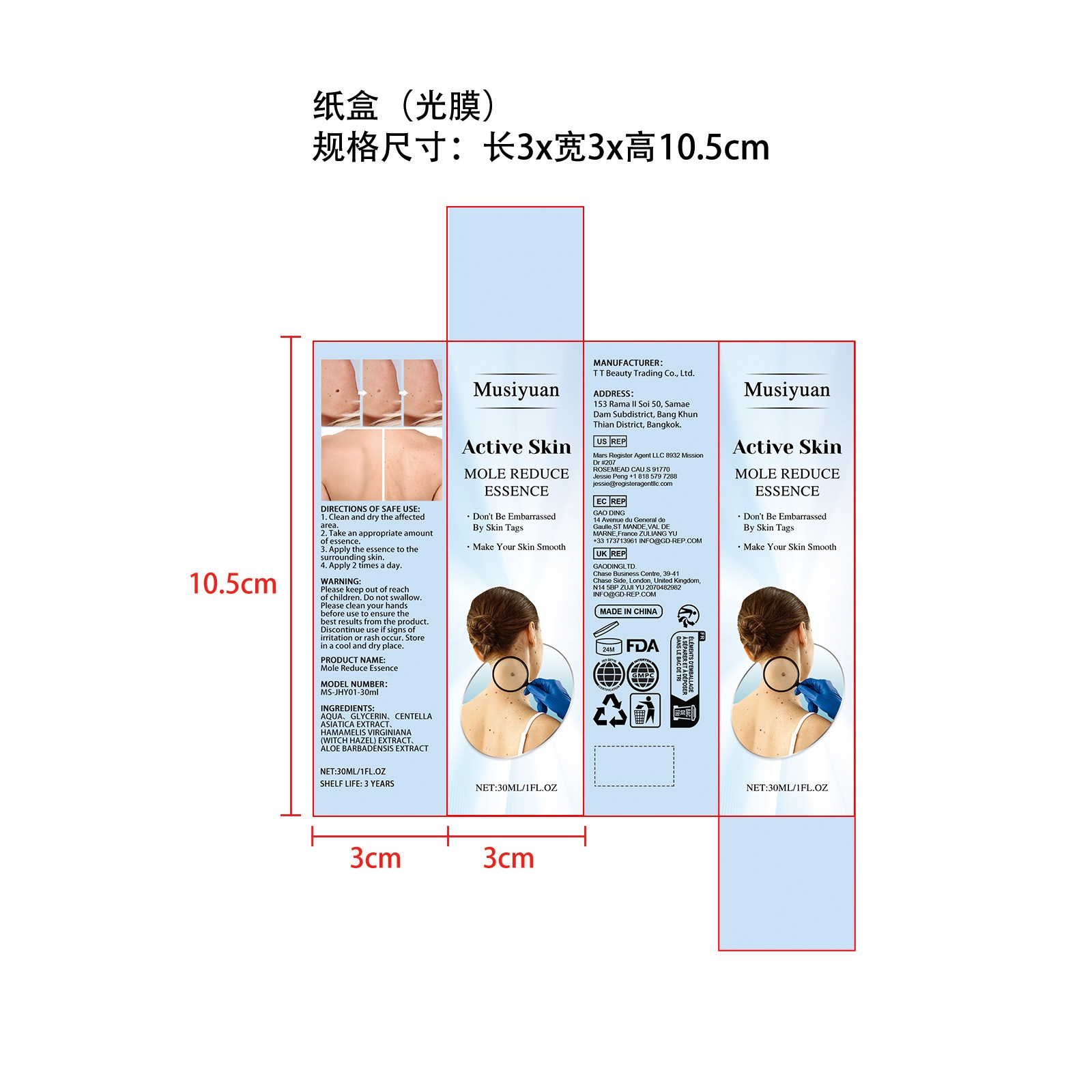 DRUG LABEL: Mole Reduce Essence
NDC: 85206-009 | Form: LIQUID
Manufacturer: TT Beauty Trading Co., Ltd.
Category: otc | Type: HUMAN OTC DRUG LABEL
Date: 20251102

ACTIVE INGREDIENTS: ALOE BARBADENSIS LEAF 0.006 mg/30 mg; CENTELLA ASIATICA LEAF 0.06 mg/30 mg; HAMAMELIS VIRGINIANA (WITCH HAZEL) LEAF WATER 0.006 mg/30 mg
INACTIVE INGREDIENTS: GLYCERIN 1.2 mg/30 mg; AQUA 28.728 mg/30 mg

ACTIVE INGREDIENT

CENTELLA ASIATICA EXTRACT、
HAMAMELIS VIRGINIANA (WITCH HAZEL) EXTRACT、
ALOE BARBADENSIS EXTRACT

PURPOSE

Don't Be Embarrassed By Skin Tags.

Make Your Skin Smooth.

WHEN USING

1. Clean and dry the affected area. 2. Take an appropriate amount of essence. 3. Apply the essence to the surrounding skin. 4. Apply 2 times a day.

WARNINGS

Please keep out of reach of children. Do not swallow. Please clean your hands before use to ensure the best results from the product. Discontinue use if signs of irritation or rash occur. Store in a cool and dry place.

DO NOT USE

Discontinue use if signs of irritation or rash occur.

STOP USE

Discontinue use if signs of irritation or rash occur.

KEEP OUT OF REACH OF CHILDREN

Please keep out of reach of children. Do not swallow.

STORAGE AND HANDLING

Store in a cool and dry place.

INACTIVE INGREDIENT

AQUA、
GLYCERIN

DOSAGE AND ADMINISTRATION

1. Clean and dry the affected area. 2. Take an appropriate amount of essence. 3. Apply the essence to the surrounding skin. 4. Apply 2 times a day.

INDICATIONS AND USAGE

1. Clean and dry the affected area. 2. Take an appropriate amount of essence. 3. Apply the essence to the surrounding skin. 4. Apply 2 times a day.